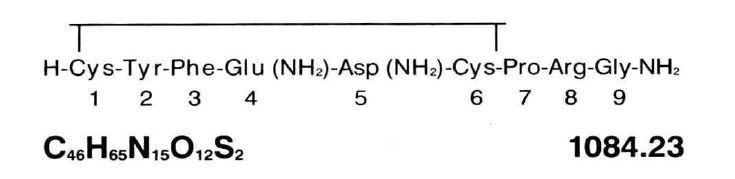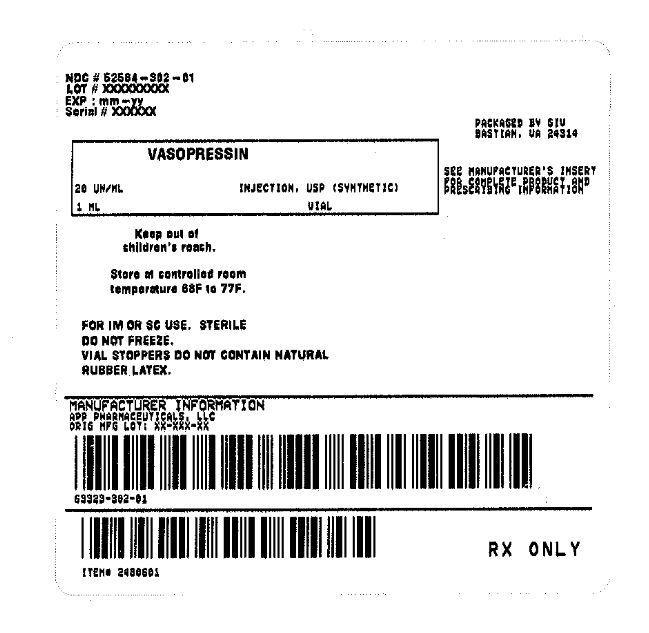 DRUG LABEL: VASOPRESSIN
NDC: 52584-302 | Form: INJECTION, SOLUTION
Manufacturer: Feneral Injectables & Vaccines, Inc
Category: prescription | Type: HUMAN PRESCRIPTION DRUG LABEL
Date: 20170123

ACTIVE INGREDIENTS: VASOPRESSIN 20 [USP'U]/1 mL
INACTIVE INGREDIENTS: CHLOROBUTANOL 5 mg/1 mL; ACETIC ACID; SODIUM HYDROXIDE

VASOPRESSIN INJECTION, USP (SYNTHETIC)

DESCRIPTION:

Vasopressin Injection, USP is a sterile solution of synthetic vasopressin of the posterior pituitary gland for intramuscular (IM) or subcutaneous use. It is substantially free from the oxytocic principle and is standardized to contain 20 pressor units/mL. The chemical name is Vasopressin, 8-L-arginine and has the following structural formula:

Each mL contains: 20 USP Vasopressin Units, chlorobutanol (anhydrous) 5 mg as preservative; Water for Injection q.s. Glacial acetic acid and/or sodium hydroxide may have been added for pH adjustment (2.4-4.5).

CLINICAL PHARMACOLOGY:

The antidiuretic action of vasopressin is ascribed to increasing reabsorption of water by the renal tubules.

Vasopressin can cause contraction of smooth muscle of the gastrointestinal tract and of all parts of the vascular bed, especially the capillaries, small arterioles and venules with less effect on the smooth musculature of the large veins. The direct effect on the contractile elements is neither antagonized by adrenergic blocking agents nor prevented by vascular denervation.

Following subcutaneous or intramuscular administration of vasopressin injection, the duration of antidiuretic activity is variable but effects are usually maintained for 2 to 8 hours.

The majority of a dose of vasopressin is metabolized and rapidly destroyed in the liver and kidneys. Vasopressin has a plasma half-life of about 10 to 20 minutes. Approximately 5% of a subcutaneous dose of vasopressin is excreted in urine unchanged after 4 hours.

INDICATIONS AND USAGE:

Vasopressin Injection, USP is indicated for prevention and treatment of postoperative abdominal distention, in abdominal roentgenography to dispel interfering gas shadows and in diabetes insipidus.

CONTRAINDICATIONS:

Anaphylaxis or hypersensitivity to the drug or its components.

WARNINGS:

This drug should not be used in patients with vascular disease, especially disease of the coronary arteries, except with extreme caution. In such patients, even small doses may precipitate anginal pain, and with larger doses, the possibility of myocardial infarction should be considered.

Vasopressin may produce water intoxication. The early signs of drowsiness, listlessness and headaches should be recognized to prevent terminal coma and convulsions.

PRECAUTIONS

General

Vasopressin should be used cautiously in the presence of epilepsy, migraine, asthma, heart failure or any state in which a rapid addition to extracellular water may produce hazard for an already overburdened system.

Chronic nephritis with nitrogen retention contraindicates the use of vasopressin until reasonable nitrogen blood levels have been attained.

Information for Patients

Side effects such as blanching of skin, abdominal cramps, and nausea may be reduced by taking 1 or 2 glasses of water at the time of vasopressin administration. These side effects are usually not serious and probably will disappear within a few minutes.

Laboratory Tests

Electrocardiograms (ECG) and fluid and electrolyte status determinations are recommended at periodic intervals during therapy.

Drug Interactions

The following drugs may potentiate the antidiuretic effect of vasopressin when used concurrently: carbamazepine; chlorpropamide; clofibrate; urea; fludrocortisone; tricyclic antidepressants.

The following drugs may decrease the antidiuretic effect of vasopressin when used concurrently: demeclocycline; norepinephrine; lithium; heparin; alcohol.

Ganglionic blocking agents may produce a marked increase in sensitivity to the pressor effects of vasopressin.

Pregnancy Category C

Animal reproduction studies have not been conducted with vasopressin. It is also not known whether vasopressin can cause fetal harm when administered to a pregnant woman or can affect reproduction capacity. Vasopressin should be given to a pregnant woman only if clearly needed.

Labor and Delivery

Doses of vasopressin sufficient for an antidiuretic effect are not likely to produce tonic uterine contractions that could be deleterious to the fetus or threaten the continuation of the pregnancy.

Nursing Mothers

Caution should be exercised when vasopressin is administered to a nursing woman.

ADVERSE REACTIONS:

Local or systemic allergic reactions may occur in hypersensitive individuals. The following side effects have been reported following the administration of vasopressin:

Body as a Whole

Anaphylaxis (cardiac arrest and/or shock) has been observed shortly after injection of vasopressin.

Cardiovascular

Cardiac arrest, circumoral pallor, arrhythmias, decreased cardiac output, angina, myocardial ischemia, peripheral vasoconstriction, and gangrene.

Gastrointestinal

Abdominal cramps, nausea, vomiting, passage of gas.

Nervous System

Tremor, vertigo, "pounding" in head.

Respiratory

Bronchial constriction.

Skin and Appendages

Sweating, urticaria, cutaneous gangrene.

Overdosage

Water intoxication may be treated with water restriction and temporary withdrawal of vasopressin until polyuria occurs. Severe water intoxication may require osmotic diuresis with mannitol, hypertonic dextrose, or urea alone or with furosemide.

DOSAGE AND ADMINISTRATION:

Vasopressin Injection may be administered IM or subcutaneously.

Ten units (0.5 mL) of Vasopressin Injection will usually elicit full physiologic response in adult patients; 5 units (0.25 mL) will be adequate in many cases. Vasopressin Injection should be given IM at three or four hour intervals as needed. The dosage should be proportionately reduced for pediatric patients. (For an additional discussion of dosage, consult the sections below.)

When determining the dose of Vasopressin Injection for a given case, the following should be kept in mind:

It is particularly desirable to give a dose not much larger than is just sufficient to elicit the desired physiologic response. Excessive doses may cause undesirable side effects-blanching of the skin, abdominal cramps, nausea-which, though not serious, may be alarming to the patient. Spontaneous recovery from such side effects occurs in a few minutes. It has been found that one or two glasses of water given at the time Vasopressin Injection is administered reduces such symptoms.

Abdominal Distention

In the average postoperative adult patient, give 5 units (0.25 mL) initially, increase to 10 units (0.5 mL) at subsequent injections if necessary. It is recommended that Vasopressin Injection be given IM and that injections be repeated at three or four hour intervals as required. Dosage to be reduced proportionately for pediatric patients.

Vasopressin Injection used in this manner will frequently prevent, or relieve, postoperative distention. These recommendations apply also to distention complicating pneumonia or other acute toxemias.

Abdominal Roentgenography

For the average case, two injections of 10 units (0.5 mL) each are suggested. These should be given two hours and one-half hour, respectively, before films are exposed. Many roentgenologists advise giving an enema prior to the first dose of Vasopressin Injection.

Diabetes Insipidus

Vasopressin Injection may be given by injection or administered intranasally on cotton pledgets, by nasal spray, or by dropper. The dose by injection is 5 to 10 units (0.25 to 0.5 mL) repeated two or three times daily as needed. When Vasopressin Injection is administered intranasally by spray or on pledgets, the dosage and interval between treatments must be determined for each patient.

Parenteral drug products should be inspected visually for paticulate matter and discoloration prior to administration, whenever solution and container permit.

HOW SUPPLIED:

Product No. | NDC No.
30201 | 63323-302-01 | Vasopressin Injection, USP 20 units, 1 mL in a 2 mL flip-top vial in packages of 25.

Store at 20° to 25°C (68° to 77°F) [see USP Controlled Room Temperature].

Do not freeze.

Vial stoppers do not contain natural rubber latex.

APP

APP PHARMACEUTICALS, LLC

Schaumburg, IL 60173

45875E

Revised: March 2010